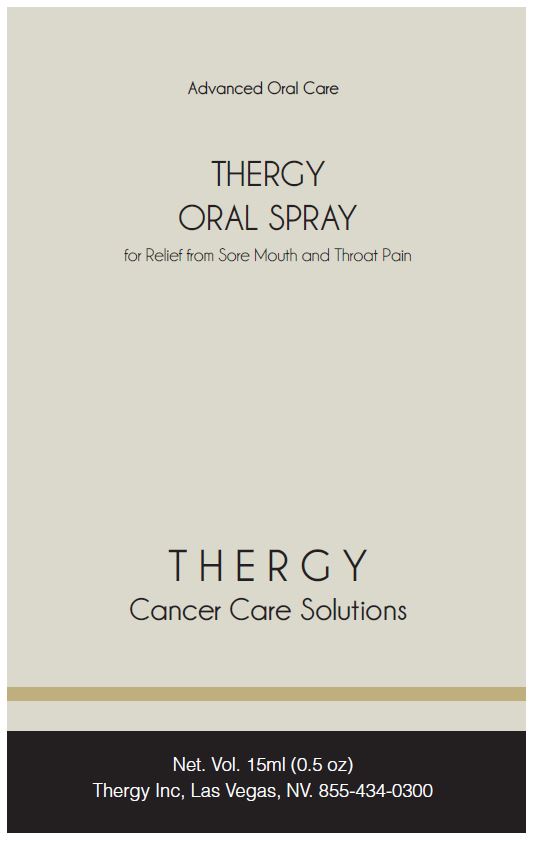 DRUG LABEL: Thergy
NDC: 69148-002 | Form: SPRAY
Manufacturer: Anjon Biologics, Inc.
Category: otc | Type: HUMAN OTC DRUG LABEL
Date: 20220201

ACTIVE INGREDIENTS: THYMOL 0.05 g/100 mL
INACTIVE INGREDIENTS: CROTON LECHLERI WHOLE; WATER; GLYCERIN; GLYCYRRHIZA GLABRA LEAF; HONEY; LAVANDULA ANGUSTIFOLIA WHOLE; SALVIA OFFICINALIS WHOLE

ANJON BIOLOGICS - THERGY (69148-002)

Drug Facts

Active Ingredients

Thymol 0.05%

Purpose

Oral Analgesic/Antimicrobial

INDICATIONS AND USAGE

Uses: Relieves sore throat pain, pain associated with canker sores, inflamed throat and mouth tissue, encourage healing of irritated mouth and throat sores and helps to reduce infection.

WARNINGS

Warnings: Stop use and ask your dentist or doctor if swelling, rash or fever develops.

KEEP OUT OF REACH OF CHILDREN

Keep out of reach of childrenDo not administer to children under 3 years of age unless directed by your doctor.

DOSAGE AND ADMINISTRATION

Directions: For oral use only as directed by your health care professional. Shake gently prior to each use. Open mouth wide and insert applicator into mouth. Spray 2 to 3 pump sprays into mouth and throat area then swallow. Repeat every few hours or as needed.

Other Information for cancer patients: For use by cancer patients being treated with chemotherapy and/or radiation. For relief of lesions of the oral cavity associated with Muscositis. Safe and effective treatment for muscitis pain in patients with cancer. Spray in mouth, let stand for a few seconds then swallow.

Other Information: This formula is dark red in color and may temporarily color the mouth area. This is normal.

STORAGE AND HANDLING

Store between 20-25 °C (68-77°F). Do not refrigerate

INACTIVE INGREDIENT

Inactive Ingredients: Croton Lechleri, Deionized Water, Glycerin, Glycyrrhiza Leaf Extract, Honey, Lavandula Angustifolia Extract, Salvia Officinalis